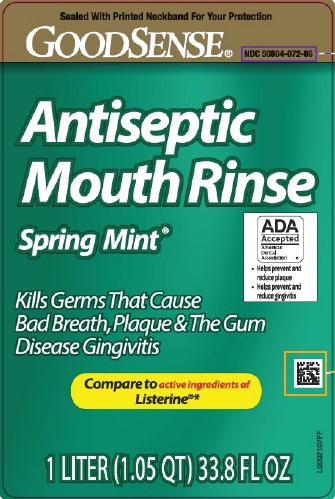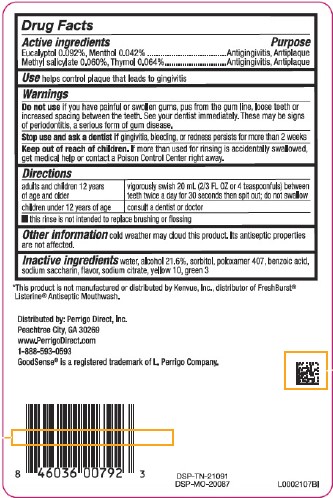 DRUG LABEL: Antiseptic Mouth Rinse
NDC: 50804-072 | Form: MOUTHWASH
Manufacturer: Perrigo Direct, Inc 
Category: otc | Type: HUMAN OTC DRUG LABEL
Date: 20260219

ACTIVE INGREDIENTS: EUCALYPTOL 0.92 mg/1 mL; MENTHOL 0.42 mg/1 mL; METHYL SALICYLATE 0.6 mg/1 mL; THYMOL 0.64 mg/1 mL
INACTIVE INGREDIENTS: WATER; ALCOHOL; SORBITOL; POLOXAMER 407; BENZOIC ACID; SACCHARIN SODIUM; SODIUM CITRATE; D&C YELLOW NO. 10; FD&C GREEN NO. 3

Good Sense 072.003/072AL rev2-AN
Spring Mint Antiseptic Mouthrinse

Active Ingredients

Eucalyptol 0.092%

Menthol 0.042%

Methyl salicylate 0.060%

Thymol 0.064%

Purpose

Antigingivitis, Antiplaque

Use

helps control plaque that leads to gingivitis

Warnings

for this product

Do not use

if you have painful or swollen gums, pus from the gum line, loose teeth or increased spacing between the teeth. See your dentist immediately. These may be signs of periodontitis, a serious form of gum disease.

Stop use and ask a dentist if

gingivitis, bleeding, or redness persists for more than 2 weeks.

Keep out of reach of children.

If more than used for rinsing is accidentally swallowed, get medical help or contact a Poison Control Center right away.

Directions

Adults and children 12 years of age and older - vigorously swish 20 ml (2/3 FL OZ or 4 teaspoonfuls) between teeth twice a day for 30 seconds then spit out; do not swallow
Children under 12 years of age - consult a dentist or doctor

- This rinse is not intended to replace brushing or flossing

Other information

cold weather may cloud this product. Its antiseptic properties are not affected.

Inactive ingredients

water, alcohol 21.6%, sorbitol, poloxamer 407, benzoic acid, sodium saccharin, flavor, sodium citrate, yellow 10, green 3

Disclaimer

*This product is not manufactured or distributed by Kenvue, Inc., distributor of FreshBurst®ListerineAntiseptic Mouthwash.

ADVERSE REACTION

Distributed by: Perrigo Direct, Inc.

Peachtree City, GA 30269

www.PerrigoDirect.com

1-888-593-0593

GoodSense® is a registered trademark of L. Perrigo Company.

DSP-TN-21091

DSP-MO-20087

Principal Panel Display

Sealed With Printed Neckband For your Protection

GoodSense®

NDC 50804-072-86

ANTISEPTIC MOUTH RINSE

Spring Mint®

ADA Accepted

American Dental Association

- Helps prevent and reduce plaque
- Helps prevent and reduce gingivitis

Kills germs that cause bad breath, plaque & the gum disease gingivitis

Compare to the Active Ingredients in Listerine®*

1 LITER (1.05 QT) 33.8 FL OZ